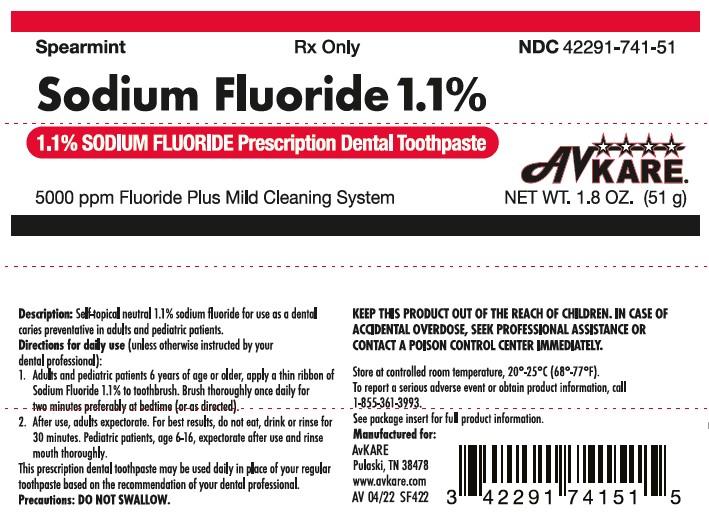 DRUG LABEL: Sodium Flouride
NDC: 42291-741 | Form: PASTE, DENTIFRICE
Manufacturer: AvKARE
Category: prescription | Type: HUMAN PRESCRIPTION DRUG LABEL
Date: 20260115

ACTIVE INGREDIENTS: SODIUM FLUORIDE 5 mg/1 mL
INACTIVE INGREDIENTS: WATER; SORBITOL; SPEARMINT; XANTHAN GUM; FD&C BLUE NO. 1; SODIUM BENZOATE; HYDRATED SILICA; TITANIUM DIOXIDE; SODIUM LAURYL SULFATE; CALCIUM PHOSPHATE, DIBASIC, ANHYDROUS; GLYCERIN; XYLITOL

Sodium Flouride 1.1%
1.1% SODIUM FLOURIDE Prescription Dental Toothpaste

Sodium Fluoride 1.1%

1.1% Sodium Fluoride Prescription Dental Toothpaste

DESCRIPTION

Self-topical neutral fluoride dentifrice containing 1.1% (w/w) sodium fluoride for use as a dental caries preventive in adults and pediatric patients.

Active Ingredient

Sodium fluoride 1.1% (w/w).

Inactive Ingredients

Dicalcium Phosphate, FD&C Blue No. 1, Flavor, Glycerin, Hydrated Silica, Purified Water, Sodium Benzoate, Sodium Lauryl Sulfate, Sorbitol, Spearmint Flavor, Titanium Dioxide, Xanthan Gum, Xylitol

CLINICAL PHARMACOLOGY

Frequent topical applications to the teeth with preparations having a relatively high fluoride content increase tooth resistance to acid dissolution and enhance penetration of the fluoride ion into tooth enamel.

INDICATIONS AND USAGE

A dental caries preventive; for once daily self-applied topical use. It is well established that 1.1% sodium fluoride is safe

and extraordinarily effective as a caries preventive when applied frequently with mouthpiece applicators.1-4 Sodium

Fluoride 1.1% in a squeeze-tube is easily applied onto a toothbrush. This prescription dental cream should

be used once daily in place of your regular toothpaste unless otherwise instructed by your dental professional. May be

used whether or not drinking water is fluoridated, since topical fluoride cannot produce fluorosis. (See WARNINGS for

exception.)

CONTRAINDICATIONS

Do not use in pediatric patients under age 6 years unless recommended by a dentist or physician.

WARNINGS

Prolonged daily ingestion may result in various degrees of dental fluorosis in pediatric patients under age 6 years,

especially if the water fluoridation exceeds 0.6 ppm, since younger pediatric patients frequently cannot perform the

brushing process without significant swallowing. Use in pediatric patients under age 6 years requires special supervision

to prevent repeated swallowing of the dental cream which could cause dental fluorosis. Read directions carefully

before using.

KEEP THIS PRODUCT OUT OF THE REACH OF CHILDREN. IN CASE OF ACCIDENTAL OVERDOSE, SEEK PROFESSIONAL ASSISTANCE OR CONTACT A POISON CONTROL CENTER IMMEDIATELY.

PRECAUTIONS

General

Not for systemic treatment. DO NOT SWALLOW.

Carcinogenesis, Mutagenesis, Impairment of Fertility

In a study conducted in rodents, no carcinogenesis was found in male and female mice and female rats treated with fluoride at dose levels ranging from 4.1 to 9.1 mg/kg of body weight. Equivocal evidence of carcinogenesis was reported in male rats treated with 2.5 and 4.1 mg/kg of body weight. In a second study, no carcinogenesis was observed in rats, males or females, treated with fluoride up to 11.3 mg/kg of body weight. Epidemiological data provide no credible evidence for an association between fluoride, either naturally occurring or added to drinking water and risk of human cancer.

Fluoride ion is not mutagenic in standard bacterial systems. It has been shown that fluoride ion has potential to induce chromosome aberrations in cultured human and rodent cells at doses much higher than those to which humans are exposed. In vivo data are conflicting. Some studies report chromosome damage in rodents, while other studies using similar protocols report negative results.

Potential adverse reproductive effects of fluoride exposure in humans has not been adequately evaluated. Adverse effects on reproduction were reported for rats, mice, fox, and cattle exposed to 100 ppm or greater concentrations of fluoride in their diet or drinking water. Other studies conducted in rats demonstrated that lower concentrations of fluoride (5 mg/kg of body weight) did not result in impaired fertility and reproductive capabilities.

Pregnancy

Teratogenic Effects

Pregnancy Category B

It has been shown that fluoride crosses the placenta of rats, but only 0.01% of the amount administered is incorporated in fetal tissue. Animal studies (rats, mice, rabbits) have shown that fluoride is not a teratogen. Maternal exposure to 12.2 mg fluoride/kg of body weight (rats) or 13.1 mg/kg of body weight (rabbits) did not affect the litter size or fetal weight and did not increase the frequency of skeletal or visceral malformations. There are no adequate and well-controlled studies in pregnant women. However, epidemiological studies conducted in areas with high levels of naturally fluoridated water showed no increase in birth defects. Heavy exposure to fluoride during in utero development may result in skeletal fluorosis which becomes evident in childhood.

Nursing Mothers

It is not known if fluoride is excreted in human milk. However, many drugs are excreted in milk, and caution should be exercised when products containing fluoride are administered to a nursing woman. Reduced milk production was reported in farm-raised fox when the animals were fed a diet containing a high concentration of fluoride (98-137 mg/kg of body weight). No adverse effects on parturition, lactation, or offspring were seen in rats administered fluoride up to 5 mg/kg of body weight.

Pediatric Use

The use of Sodium Fluoride 1.1% toothpaste in pediatric age groups 6 to 16 years as a caries preventive is supported by

pioneering clinical studies with 1.1% sodium fluoride gels in mouth trays in students age 11- 14 years conducted by

Englander, et al.2,3,4 Safety and effectiveness in pediatric patients below the age of 6 years have not been established.

Please refer to the CONTRAINDICATIONS and WARNINGS sections.

Geriatric Use

Of the total number of subjects in clinical studies of 1.1% (w/v) sodium fluoride, 15 percent were 65 and over, while 1 percent were 75 and over. No overall differences in safety or effectiveness were observed between these subjects and younger subjects, and other reported clinical experience has not identified differences in responses between the elderly and younger patients, but greater sensitivity of some older individuals cannot be ruled out. This drug is known to be substantially excreted by the kidney, and the risk of toxic reactions to this drug may be greater in patients with impaired renal function. Because elderly patients are more likely to have decreased renal function, care should be taken in dose selection, and it may be useful to monitor renal function.

ADVERSE REACTIONS

Allergic reactions and other idiosyncrasies have been rarely reported.

You should call your doctor, or dental professional for medical advise about serious adverse events. To report a serious adverse event or obtain product information, contact AvKARE at 1-855-361-3993 or FDA at 1-800-FDA-1088 (Toll Free).

OVERDOSAGE

Accidental ingestion of large amounts of fluoride may result in acute burning in the mouth and sore tongue. Nausea,

vomiting, and diarrhea may occur soon after ingestion (within 30 minutes) and are accompanied by salivation,

hematemesis, and epigastric cramping abdominal pain. These symptoms may persist for 24 hours. If less than 5 mg

fluoride/kg body weight (i.e., less than 2.3 mg fluoride/lb body weight) have been ingested, give calcium (e.g., milk)

orally to relieve gastrointestinal symptoms and observe for a few hours. If more than 5 mg fluoride/kg body weight

(i.e., more than 2.3 mg fluoride/lb body weight) have been ingested, induce vomiting, give orally soluble calcium (e.g.,

milk, 5% calcium gluconate or calcium lactate solution) and immediately seek medical assistance. For accidental

ingestion of more than 15 mg fluoride/kg of body weight (i.e., more than 6.9 mg fluoride/lb body weight), induce

vomiting and admit immediately to a hospital facility.

A treatment dose (a thin ribbon) of Sodium Fluoride 1.1% toothpaste contains 2.5 mg fluoride. A 1.8 oz. tube contains

255 mg fluoride.

DOSAGE AND ADMINISTRATION

Follow these instructions unless otherwise instructed by your dental professional:

1. Adults and pediatric patients 6 years of age or older, apply a thin ribbon of Sodium Fluoride 1.1% toothpaste to a

toothbrush. Brush thoroughly once daily for two minutes, preferably at bedtime.

2. After use, adults expectorate. For best results, do not eat, drink, or rinse for 30 minutes. Pediatric patients, age 6-16,

expectorate after use and rinse mouth thoroughly.

HOW SUPPLIED

1.8 oz. (51 g) net wt. tube

NDC# 42291-741-51

STORAGE

Store at controlled room temperature 20° - 25°C (68°-77°F).

KEEP THIS PRODUCT OUT OF REACH OF CHILDREN

Rx Only

REFERENCES

1. American Dental Association, Council on Dental Therapeutics, Fluoride compounds, In: Accepted Dental Therapeutics,

Ed. 40, Chicago, ADA, 405-407 (1984).

2. H.R. Englander et al., Clinical Anticaries Effect of Repeated Topical Sodium Fluoride Applications by Mouthpieces,

JADA, 75, 638-644 (1967).

3. H.R. Englander, et al., Residual Anticaries Effect of Repeated Topical Sodium Fluoride Applications by Mouthpieces,

JADA 78, 783-787 (1969).

4. H.R. Englander HR et al., Incremental Rates of Dental Caries After Repeated Topical Sodium Fluoride Applications in

Children With Lifelong Consumption of Fluoridated Water, JADA, 82, 354-358, (1971).

Manufactured for:

AvKare

Pulaski, TN 38478

www.avkare.com

AV 08/22